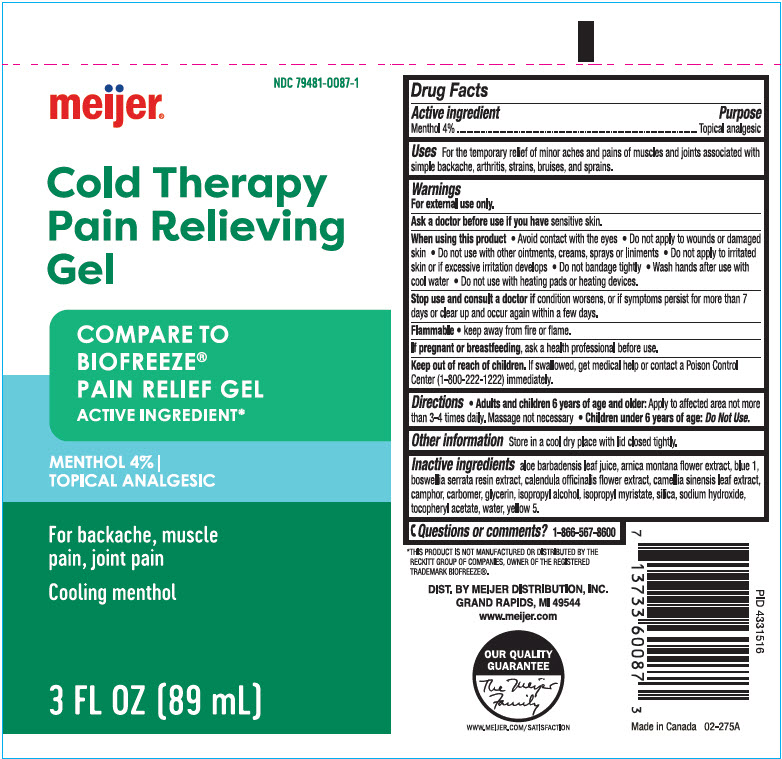 DRUG LABEL: meijer Cold Therapy Pain Relieving
NDC: 79481-0087 | Form: GEL
Manufacturer: Meijer Distribution, Inc
Category: otc | Type: HUMAN OTC DRUG LABEL
Date: 20240228

ACTIVE INGREDIENTS: MENTHOL, UNSPECIFIED FORM 40 mg/1 mL
INACTIVE INGREDIENTS: ALOE VERA LEAF; ARNICA MONTANA FLOWER; FD&C BLUE NO. 1; INDIAN FRANKINCENSE; CALENDULA OFFICINALIS FLOWER; GREEN TEA LEAF; CAMPHOR (SYNTHETIC); CARBOMER HOMOPOLYMER, UNSPECIFIED TYPE; Glycerin; Isopropyl Alcohol; Isopropyl Myristate; SILICON DIOXIDE; Sodium Hydroxide; .ALPHA.-TOCOPHEROL ACETATE, DL-; Water; FD&C YELLOW NO. 5

meijer® Cold Therapy Pain Relieving Gel
Topical analgesic

Drug Facts

Active ingredient

Menthol 4%

Purpose

Topical analgesic

Uses

For the temporary relief of minor aches and pains of muscles and joints associated with simple backache, arthritis, strains, bruises, and sprains.

Warnings

For external use only

Ask a doctor before use if you have sensitive skin.

When using this product

- Avoid contact with the eyes
- Do not apply to wounds or damaged skin
- Do not use with other ointments, creams, sprays or liniments
- Do not apply to irritated skin or if excessive irritation develops
- Do not bandage tightly
- Wash hands after use with cool water
- Do not use with heating pads or heating devices.

Stop use and consult a doctor if

- condition worsens, or if symptoms persist for more than 7 days or clear up and occur again within a few days.

Flammable

- keep away from fire or flame.

PREGNANCY OR BREAST FEEDING

If pregnant or breastfeeding, ask a health professional before use.

Keep out of reach of children. If swallowed, get medical help or contact a Poison Control Center (1-800-222-1222) immediately.

Directions

- Adults and children 6 years of age and older: Apply to affected area not more than 3-4 times daily. Massage not necessary
- Children under 6 years of age: Do Not Use.

Other information store in a cool dry place with lid closed tightly.

INACTIVE INGREDIENT

Inactive ingredients aloe barbadensis leaf juice, arnica montana flower extract, blue 1, boswellia serrata resin extract, calendula officinalis flower extract, camellia sinensis leaf extract, camphor, carbomer, glycerin, isopropyl alcohol, isopropyl myristate, silica, sodium hydroxide, tocopheryl acetate, water, yellow 5.

Questions or comments? 1-866-567-8600

DIST. BY MEIJER DISTRIBUTION, INC.
GRAND RAPIDS, MI 49544

PRINCIPAL DISPLAY PANEL - 89 mL Tube Label

NDC 79481-0087-1

meijer®

Cold Therapy
Pain Relieving
Gel

COMPARE TO
BIOFREEZE®
PAIN RELIEF GEL
ACTIVE INGREDIENT*

MENTHOL 4% |
TOPICAL ANALGESIC

For backache, muscle
pain, joint pain

Cooling menthol

3 FL OZ (89 mL)